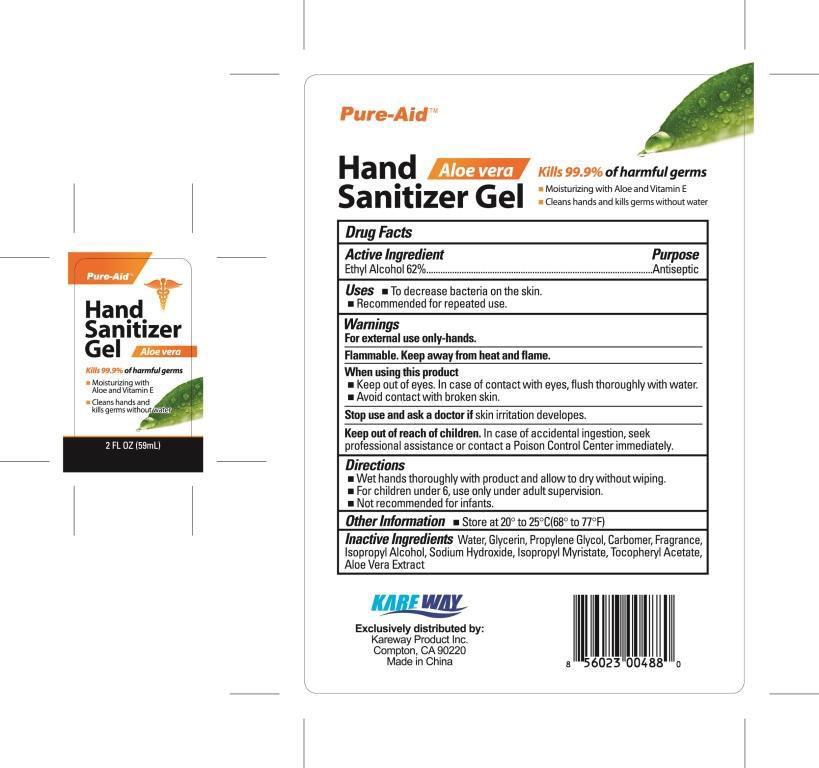 DRUG LABEL: Hand Sanitizer
NDC: 67510-0487 | Form: GEL
Manufacturer: Kareway Product, Inc.
Category: otc | Type: HUMAN OTC DRUG LABEL
Date: 20131008

ACTIVE INGREDIENTS: alcohol 62 mL/100 mL
INACTIVE INGREDIENTS: WATER; PROPYLENE GLYCOL; ALOE VERA LEAF; CARBOMER 940; GLYCERIN; .ALPHA.-TOCOPHEROL ACETATE, D-; SODIUM HYDROXIDE; ISOPROPYL ALCOHOL; ISOPROPYL MYRISTATE

Drug facts

Active Ingredient

Ethyl Alcohol 62%

Purpose

Antiseptic

Keep out of reach of children

In case of a accidental ingestion, seek professional assistance or contact a Poison control Center immediately.

Uses

- To decrease bacteria on the skin.
- Recommended for repeated use.

Warnings

For external use only-hands.
Flammable. Keep away from hear or flame.

When using this product

- Keep out of eyes. In case of contact with eyes, flush throughly with water.
- Avoid contact with broken skin.

Stop use and ask a doctor if

skin irritation developes

Directions

- Wet hands throughly with product and allow to dry without wiping.
- For children under 6, use only under adult supervision
- Not recommended for infants.

Other information

- Store at 20° to 25°C (68° to 77°F)

Inactive Ingredients

Water, Glycerin, Propylene Glycol, Carbomer, Fragrance, Isopropyl Alcohol, Sodium Hydroxide, Isopropyl Myristate, Tocopheryl Acetate, Aloe Vera Extract